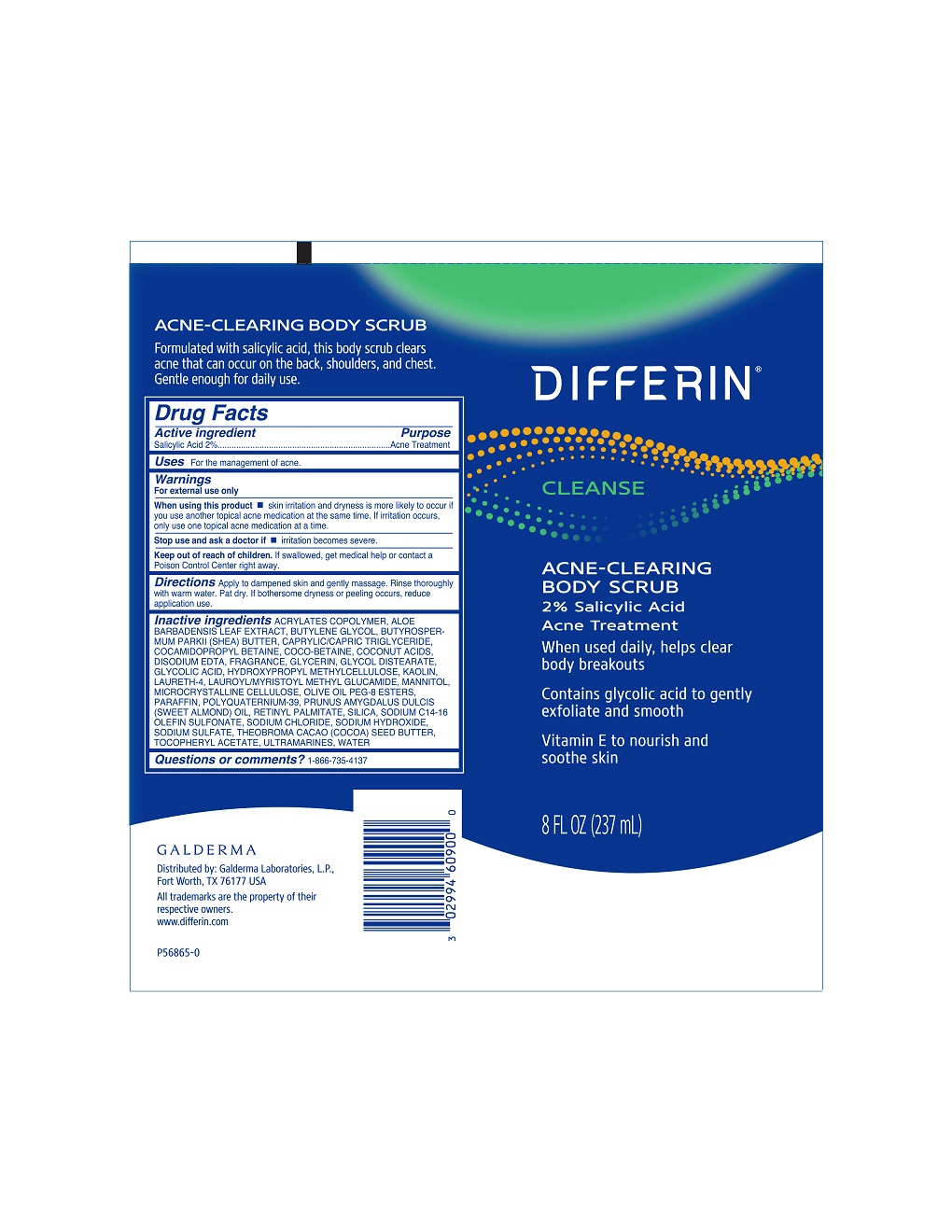 DRUG LABEL: Differin Acne Clearing Body Scrub
NDC: 0299-4609 | Form: LIQUID
Manufacturer: Galderma Laboratories, L.P.
Category: otc | Type: HUMAN OTC DRUG LABEL
Date: 20231211

ACTIVE INGREDIENTS: Salicylic Acid 20 mg/1 mL
INACTIVE INGREDIENTS: Butyl Acrylate/Methyl Methacrylate/Methacrylic Acid Copolymer (18000 Mw); Aloe Vera Leaf; Butylene Glycol; Shea Butter; Medium-Chain Triglycerides; Cocamidopropyl Betaine; Coco-Betaine; Coconut Acid; Edetate Disodium; Glycerin; Glycol Distearate; Glycolic Acid; Hypromellose, Unspecified; Kaolin; Laureth-4; Lauroyl/Myristoyl Methyl Glucamide; Mannitol; Microcrystalline Cellulose; Paraffin; Polyquaternium-39 (22.5/51/26.5 Acrylic Acid/Acrylamide/Dadmac; 1600000 Mw); Almond Oil; Vitamin A Palmitate; Silicon Dioxide; Sodium C14-16 Olefin Sulfonate; Sodium Chloride; Sodium Hydroxide; Sodium Sulfate; Cocoa Butter; .Alpha.-Tocopherol Acetate; Ultramarine Blue; Water

Drug Facts

Active Ingredient

Salicylic Acid 2%

Purpose

Acne Treatment

Use

For the management of acne

Warnings

For external use only

When using this product

- skin irritation and dryness are more likely to occur if you use another topical acne medication at the same time. If irritation occurs, only use one topical acne treatment at a time.

Stop use and ask a doctor if irritation become severe

Keep out of reach of children. If swallowed, get medical help or contact a Poison Control Center right away.

Directions

Apply to dampened skin and gently massage. Rinse thoroughly with warm water. Pat dry. If bothersome dryness or peeling occurs, reduce application use.

Inactive Ingredients

Acrylates Copolymer, Aloe Barbadensis Leaf Extract, Butylene Glycol, Butyrospermum Parkii (Shea) Butter, Caprylic/Capric Triglyceride, Cocamidopropyl Betaine, Coco-Betaine, Coconut Acids, Disodium EDTA, Fragrance, Glycerin, Glycol Distearate, Glycolic Acid, Hydroxypropyl Methylcellulose Kaolin, Laureth-4, Lauroyl/Myristoyl Methyl Glucamide, Mannitol, Microcrystalline Cellulose, Olive Oil Peg-8 Esters, Paraffin, Polyquaternium-39, Prunus Amygdalus Dulcis (Sweet Almond) Oil, Retinyl Palmitate, Salicylic Acid, Silica, Sodium C14-16 Olefin Sulfonate, Sodium Chloride, Sodium Hydroxide, Sodium Sulfate, Theobroma Cacao (Cocoa) Seed Butter, Tocopheryl Acetate, Ultramarines, Water

Question or comments? 1-866-735-4137

Distributed by: Galderma Laboratories, L.P.
Fort Worth, TX 76177 USA
All trademarks are the property of their respective owners.
differin.com
P56865-0

PRINCIPAL DISPLAY PANEL - 8 FL OZ tube

Differin®
Cleanse
ACNE-CLEARING
BODY SCRUB

2% Salicylic Acid
Acne Treatment

When used daily, helps clear
body breakouts
Contains glycolic acid to
gently exfoliate and smooth
Vitamin E to nourish and
soothe skin

8 FL OZ (237 mL)